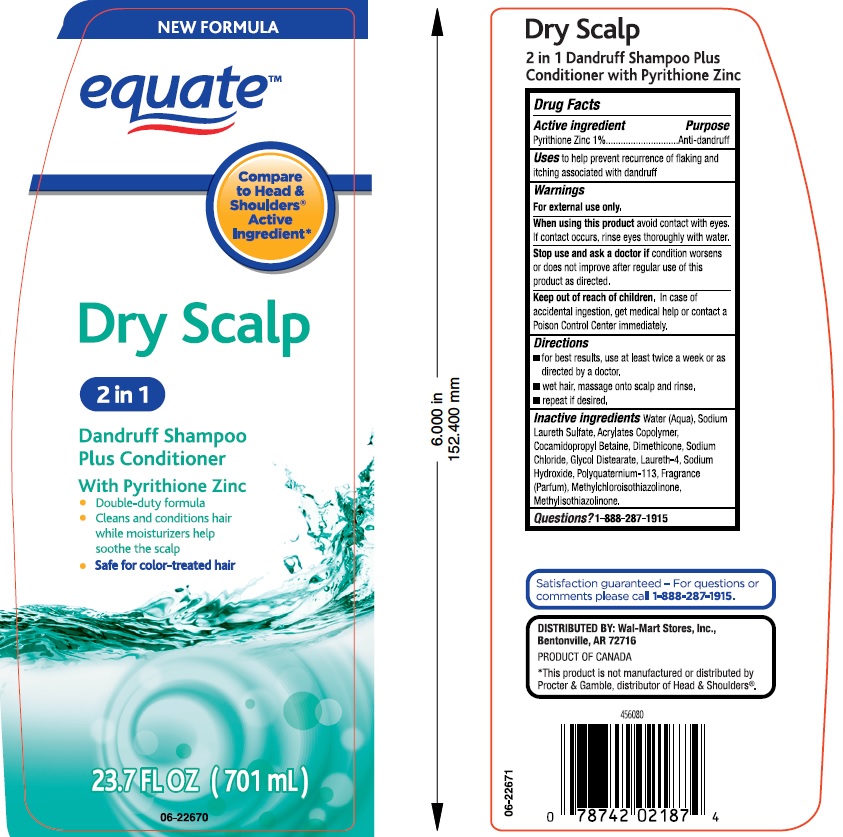 DRUG LABEL: Equate 2 in 1 Dry Scalp Dandruff
NDC: 49035-305 | Form: SHAMPOO
Manufacturer: Wal-Mart Stores, Inc.
Category: otc | Type: HUMAN OTC DRUG LABEL
Date: 20180212

ACTIVE INGREDIENTS: PYRITHIONE ZINC 10 mg/1 mL
INACTIVE INGREDIENTS: WATER; SODIUM LAURETH SULFATE; METHACRYLIC ACID - METHYL METHACRYLATE COPOLYMER (1:1); COCAMIDOPROPYL BETAINE; DIMETHICONE; SODIUM CHLORIDE; GLYCOL DISTEARATE; LAURETH-4; SODIUM HYDROXIDE; METHYLCHLOROISOTHIAZOLINONE; METHYLISOTHIAZOLINONE

Drug Facts

Active ingredient

Pyrithione Zinc 1%

Purpose

Anti-dandruff

Uses

to help prevent recurrence of flaking and itching associated with dandruff.

Warnings

For external use only.

When using this product

avoid contact with eyes. If contact occurs, rinse eyes thoroughly with water.

Stop use and ask a doctor if

condition worsens or does not improve after regular use of this product as directed

Keep out of reach of children.

In case of accidental ingestion, get medical help or contact a Poison Control Center immediately.

Directions

- for best results, use at least twice a week or as directed by a doctor.
- wet hair, massage onto scalp and rinse.
- repeat if desired.

Inactive ingredients

Water (Aqua), Sodium Laureth Sulfate, Acrylates Copolymer, Cocamidopropyl Betaine, Dimethicone, Sodium Chloride, Glycol Distearate, Laureth-4, Sodium Hydroxide, Polyquaternium-113, Fragrance (Parfum), Methylchloroisothiazolinone, Methylisothiazolinone.

Questions?

1-888-287-1915